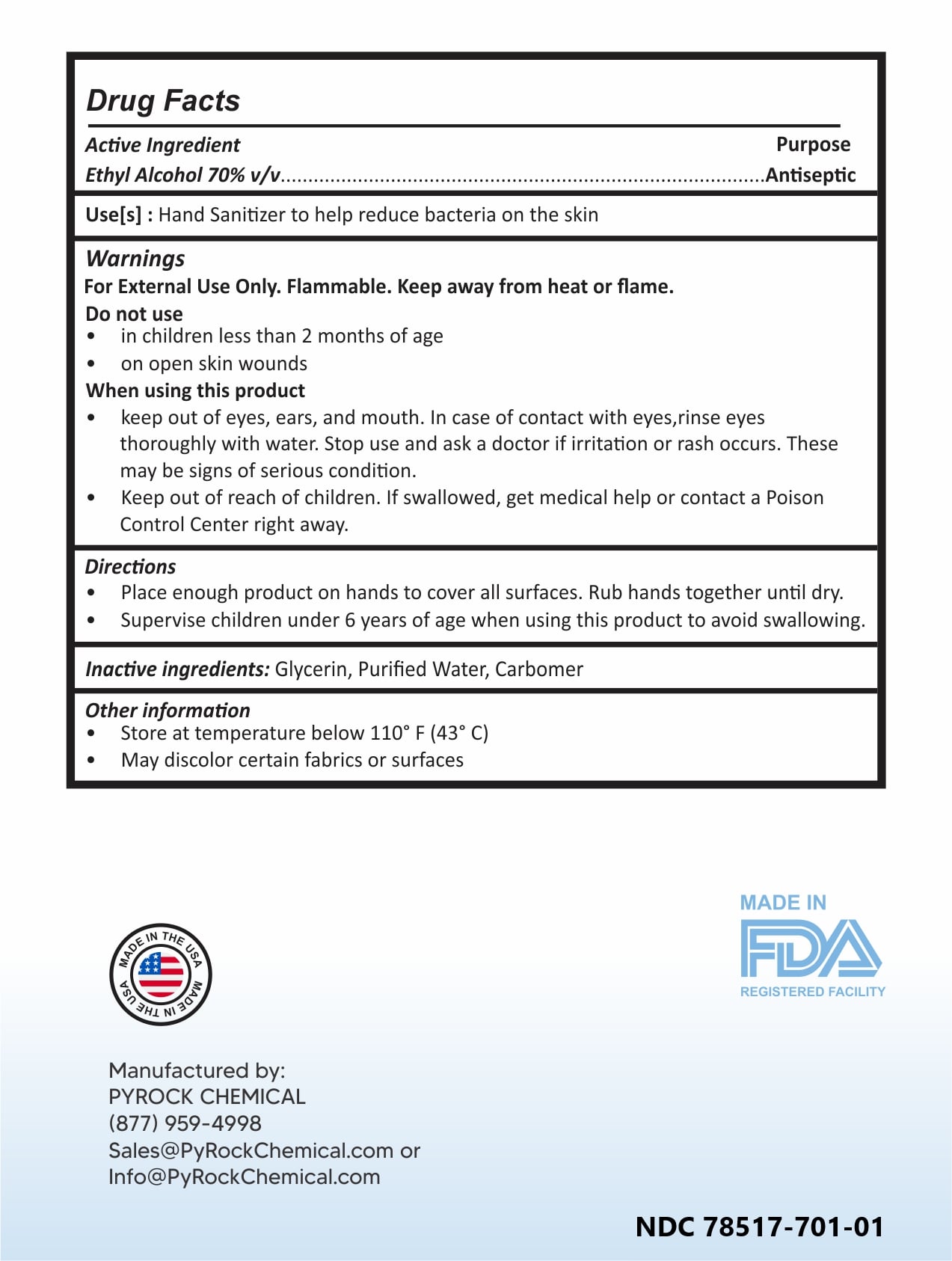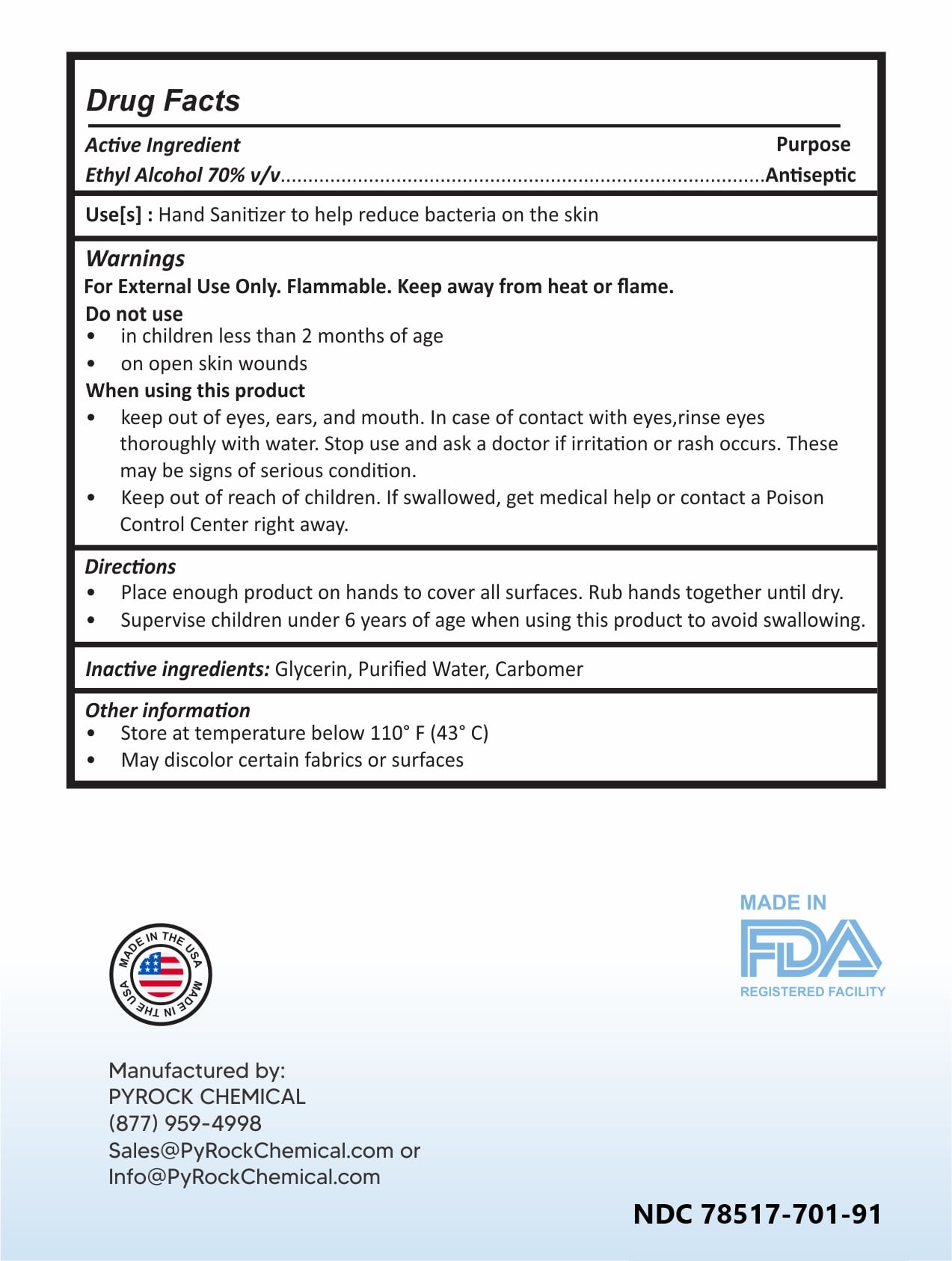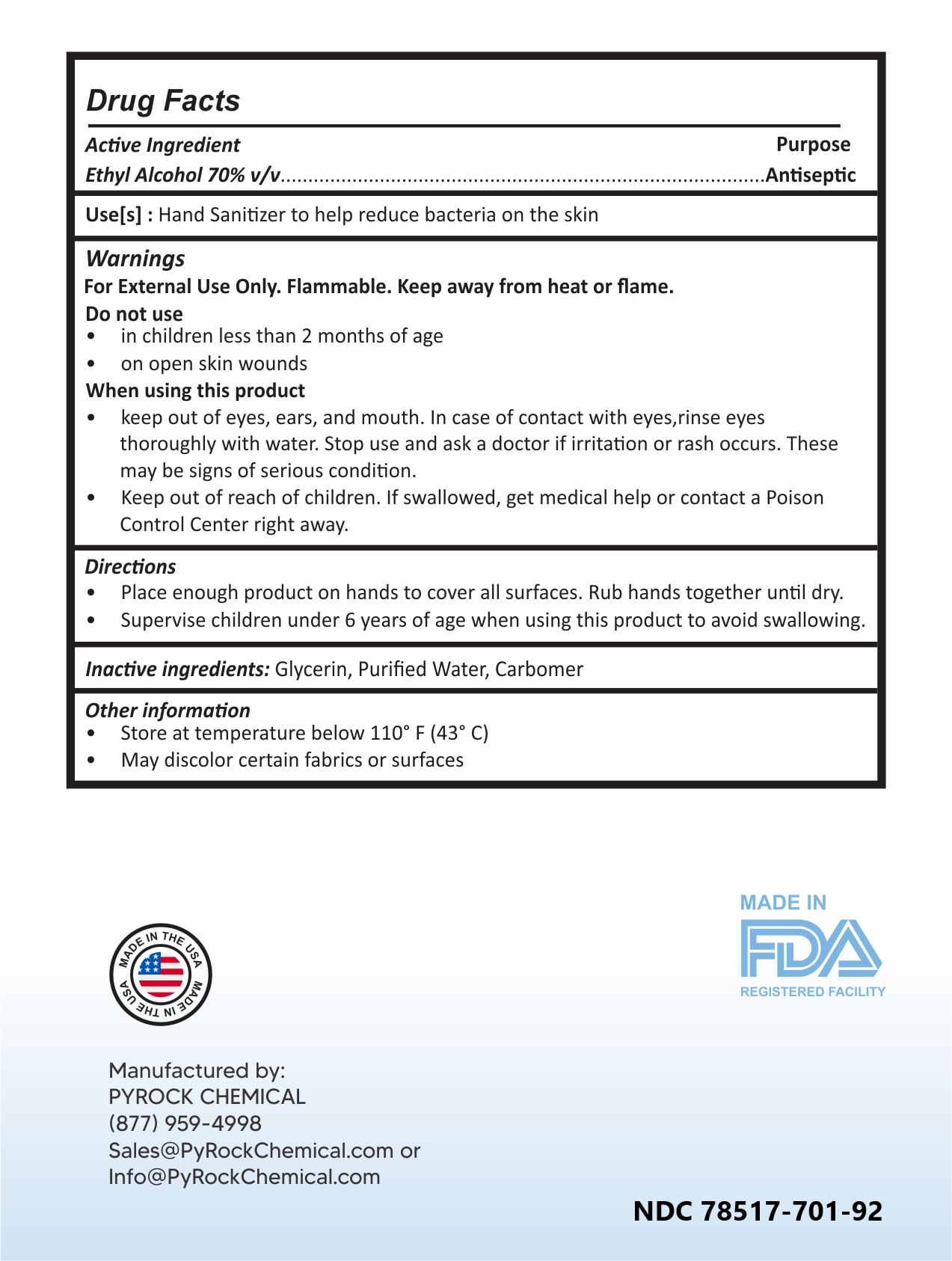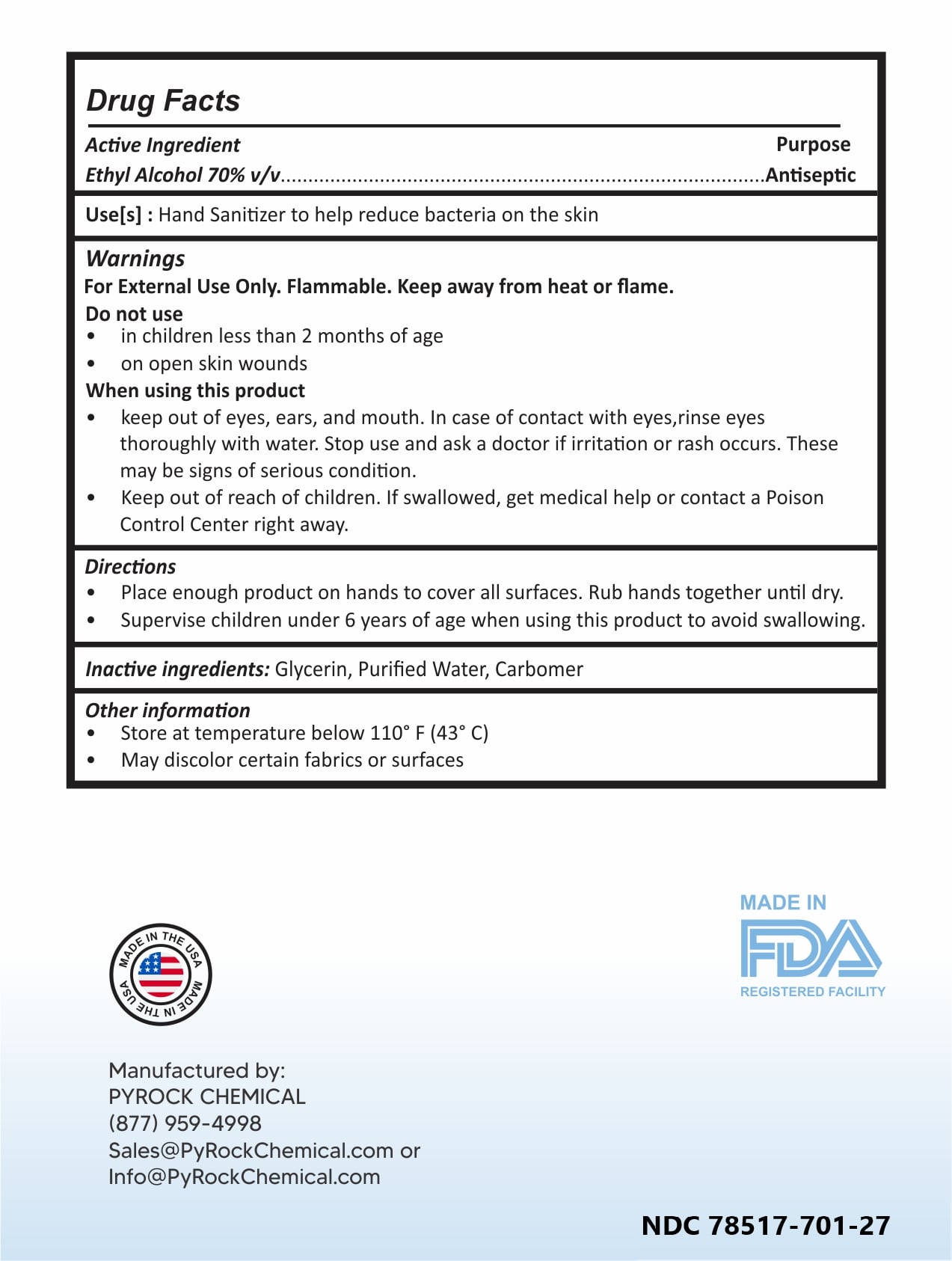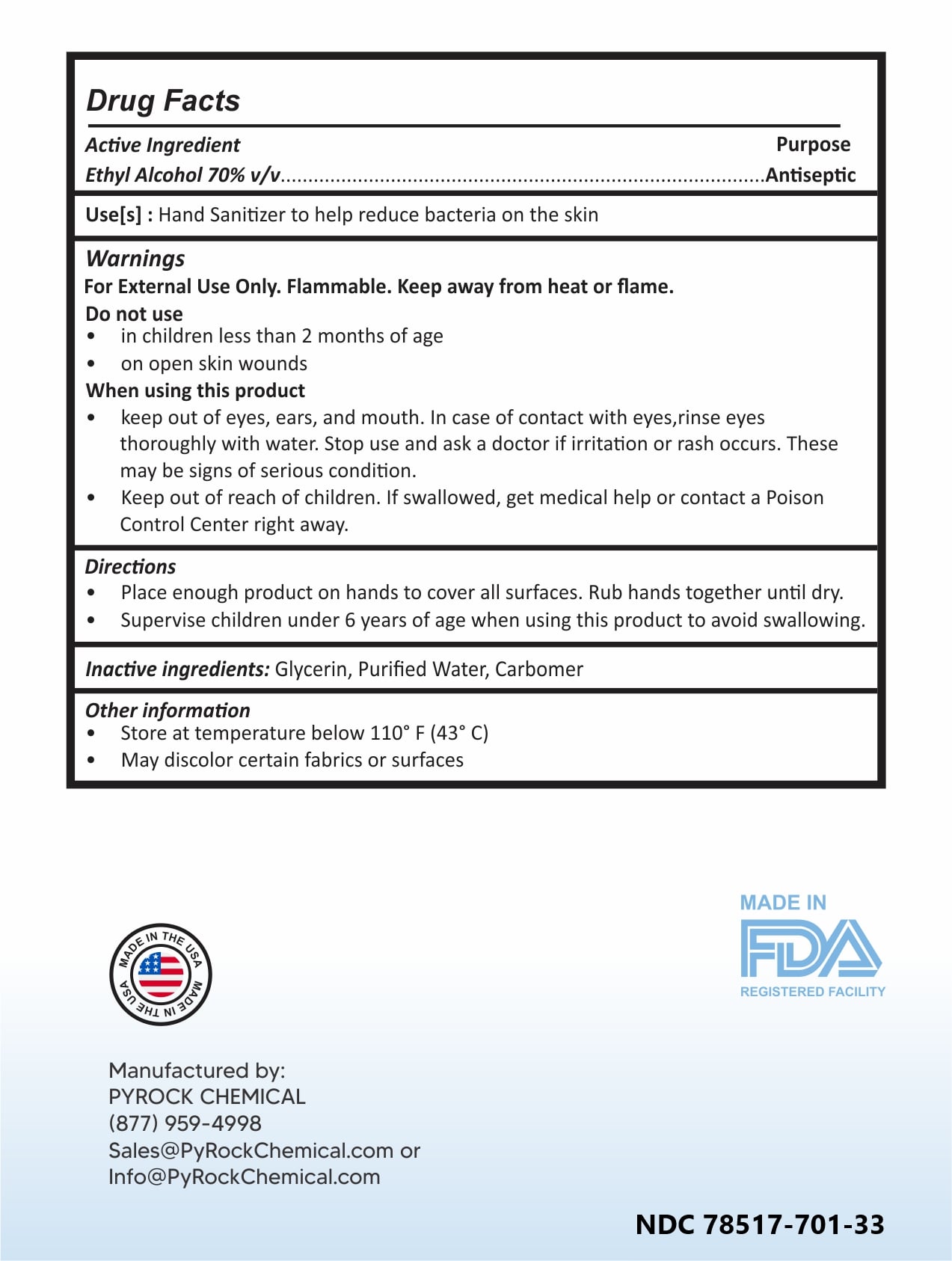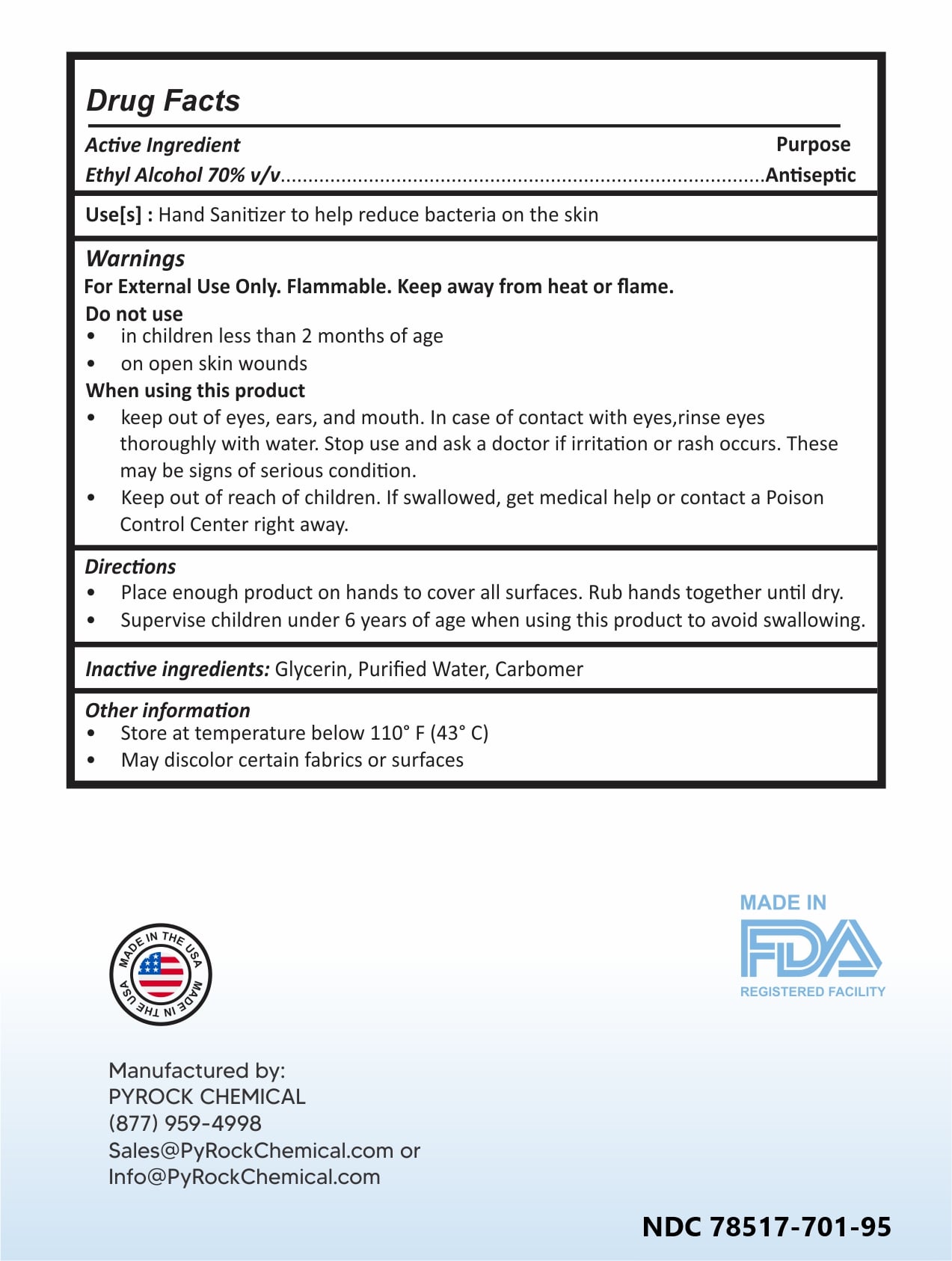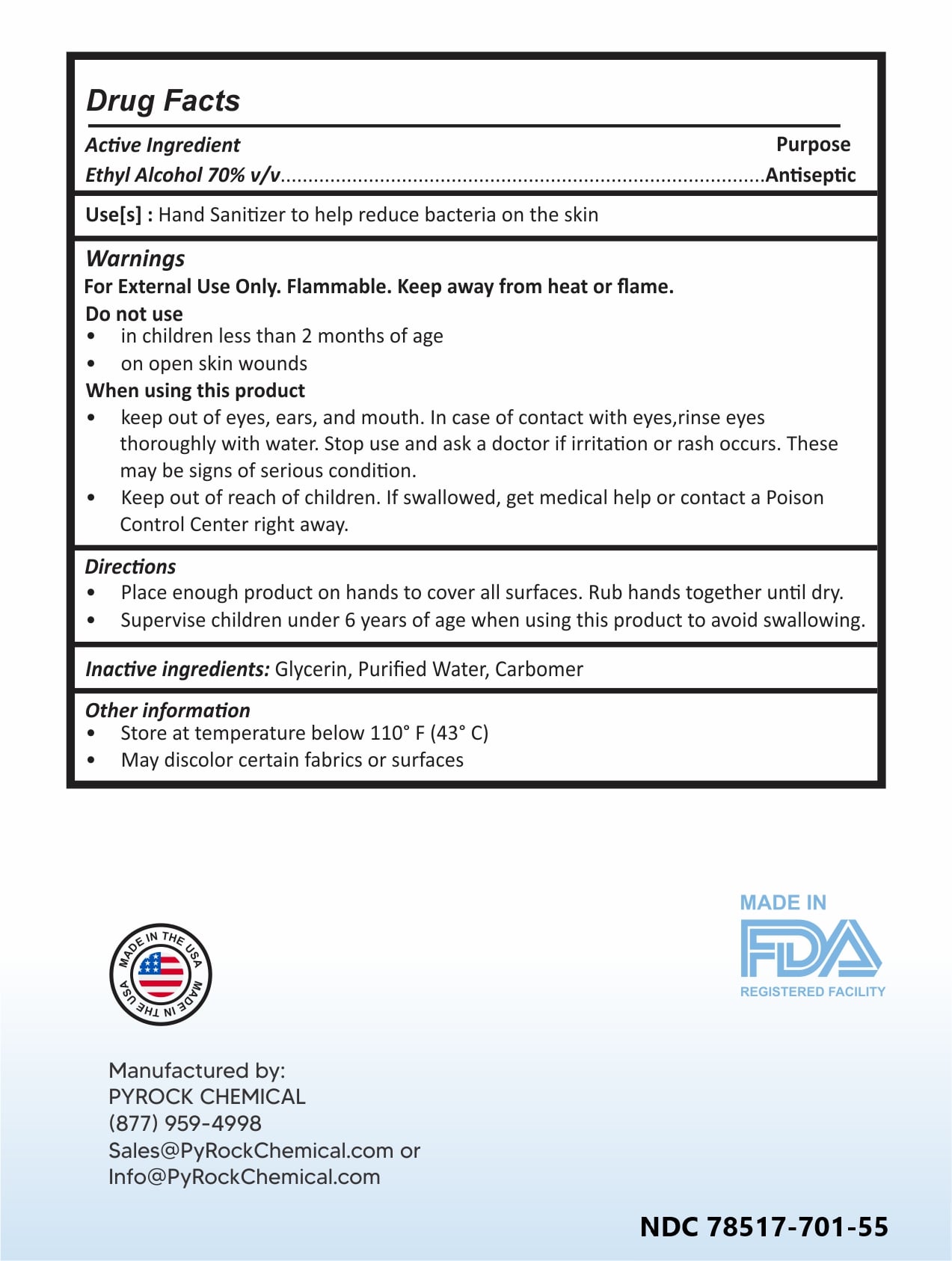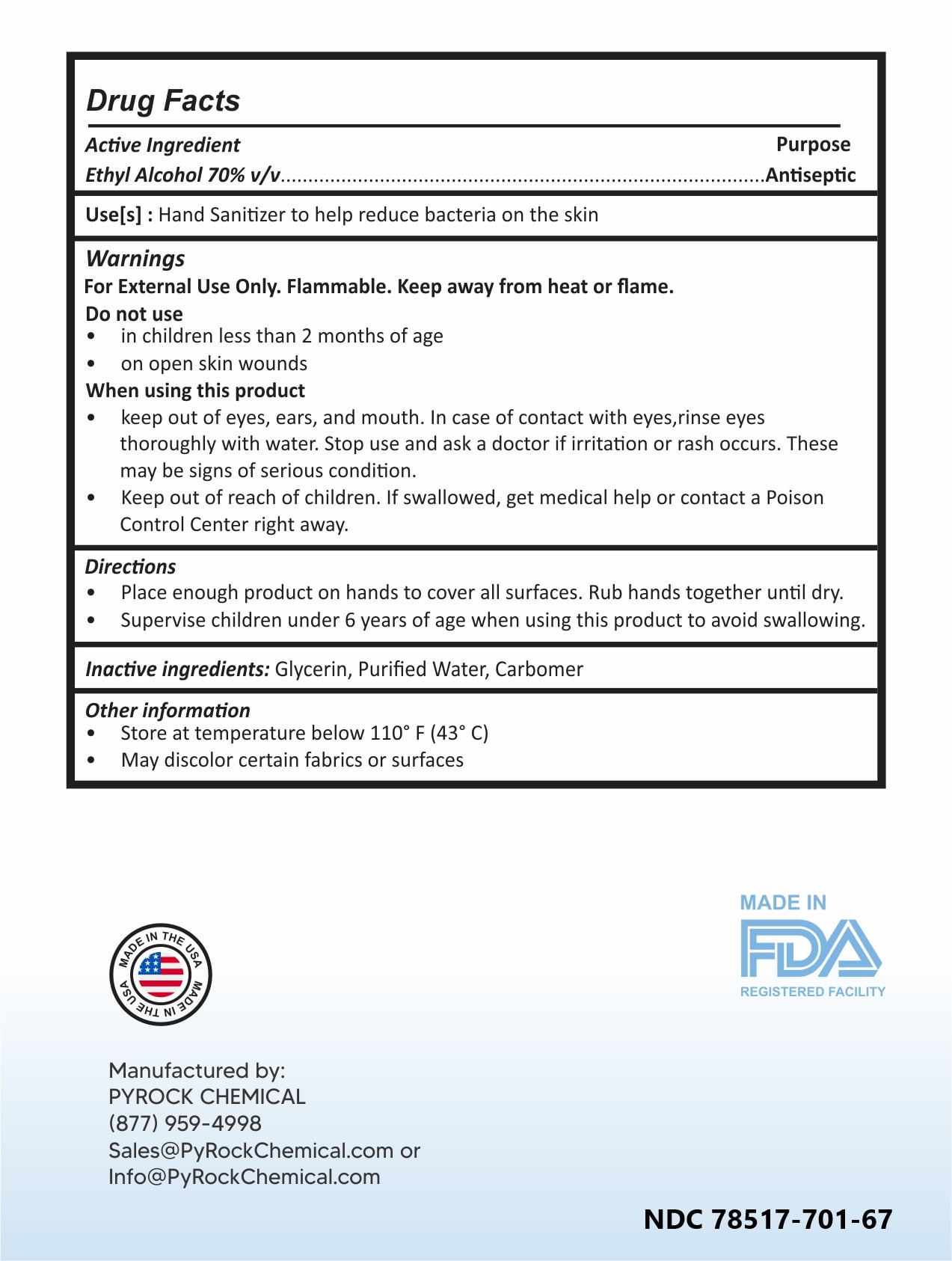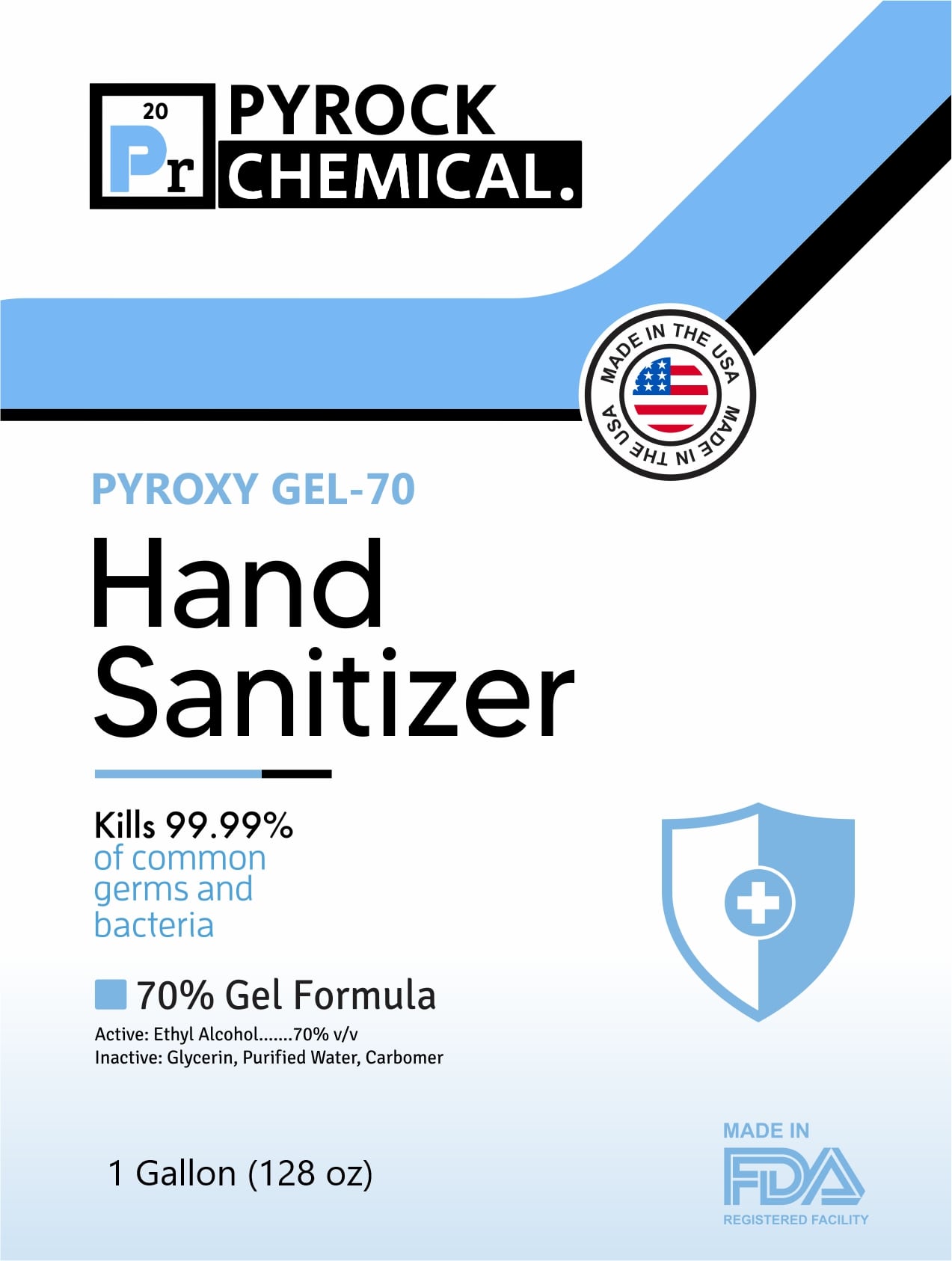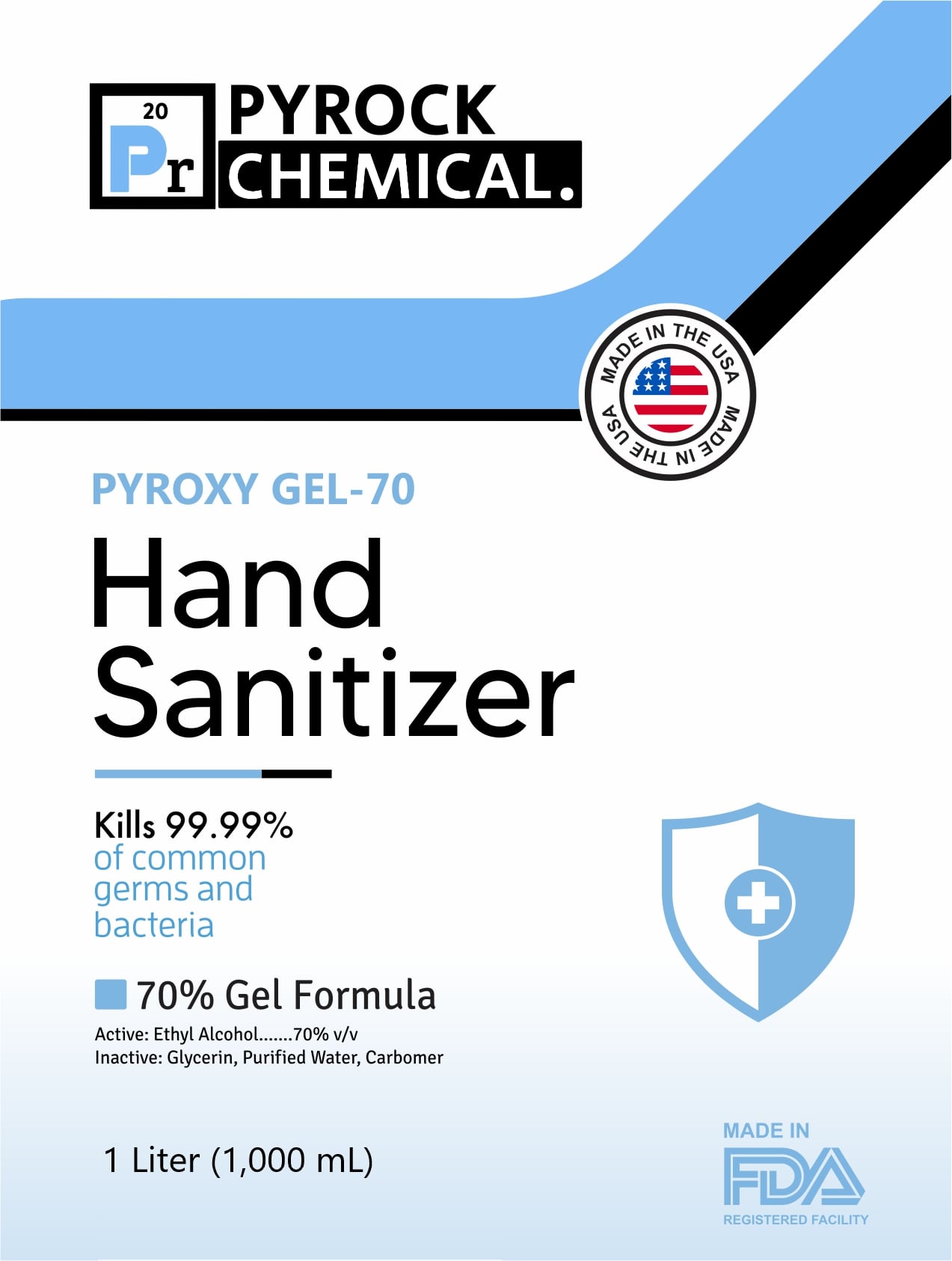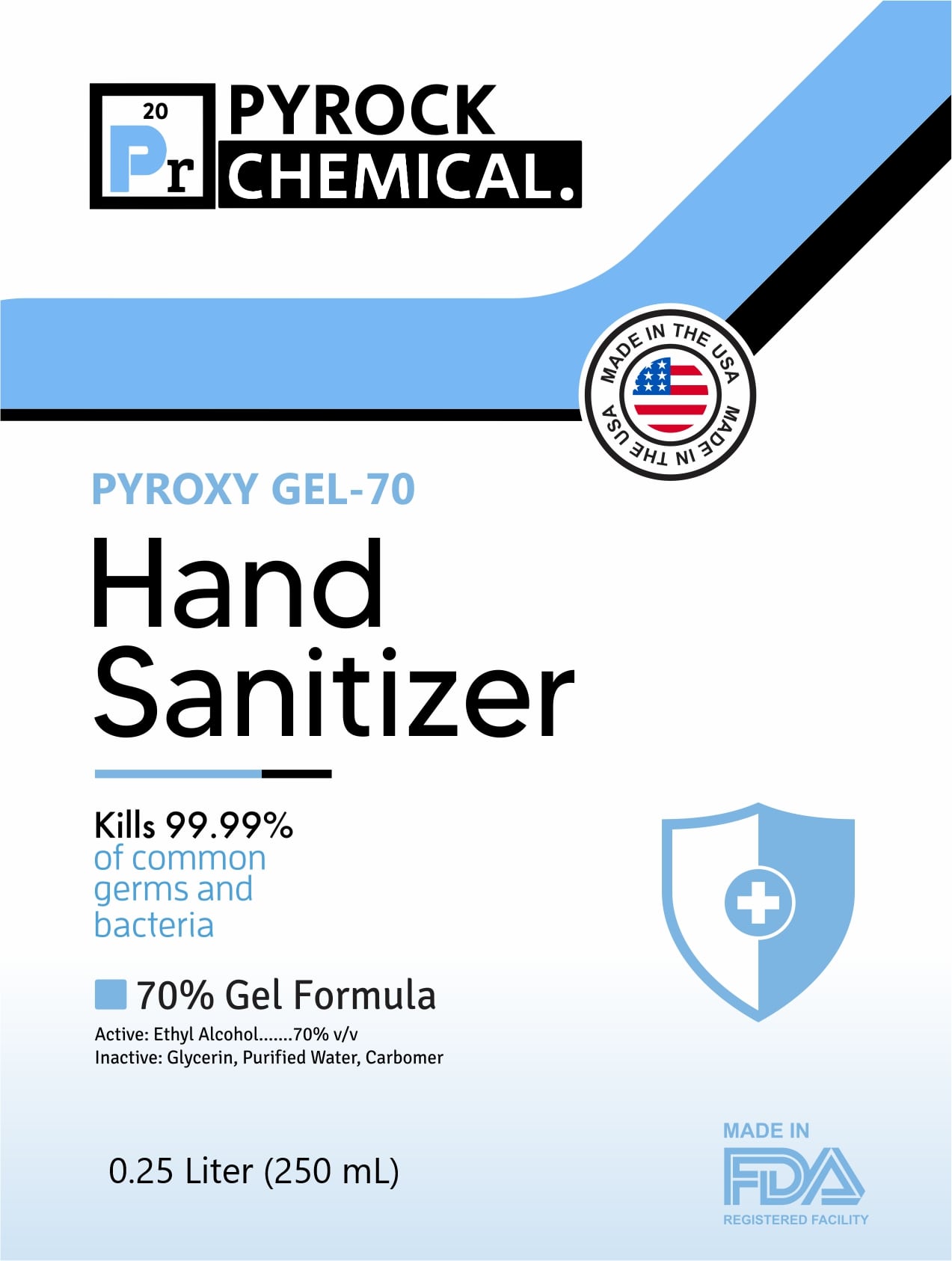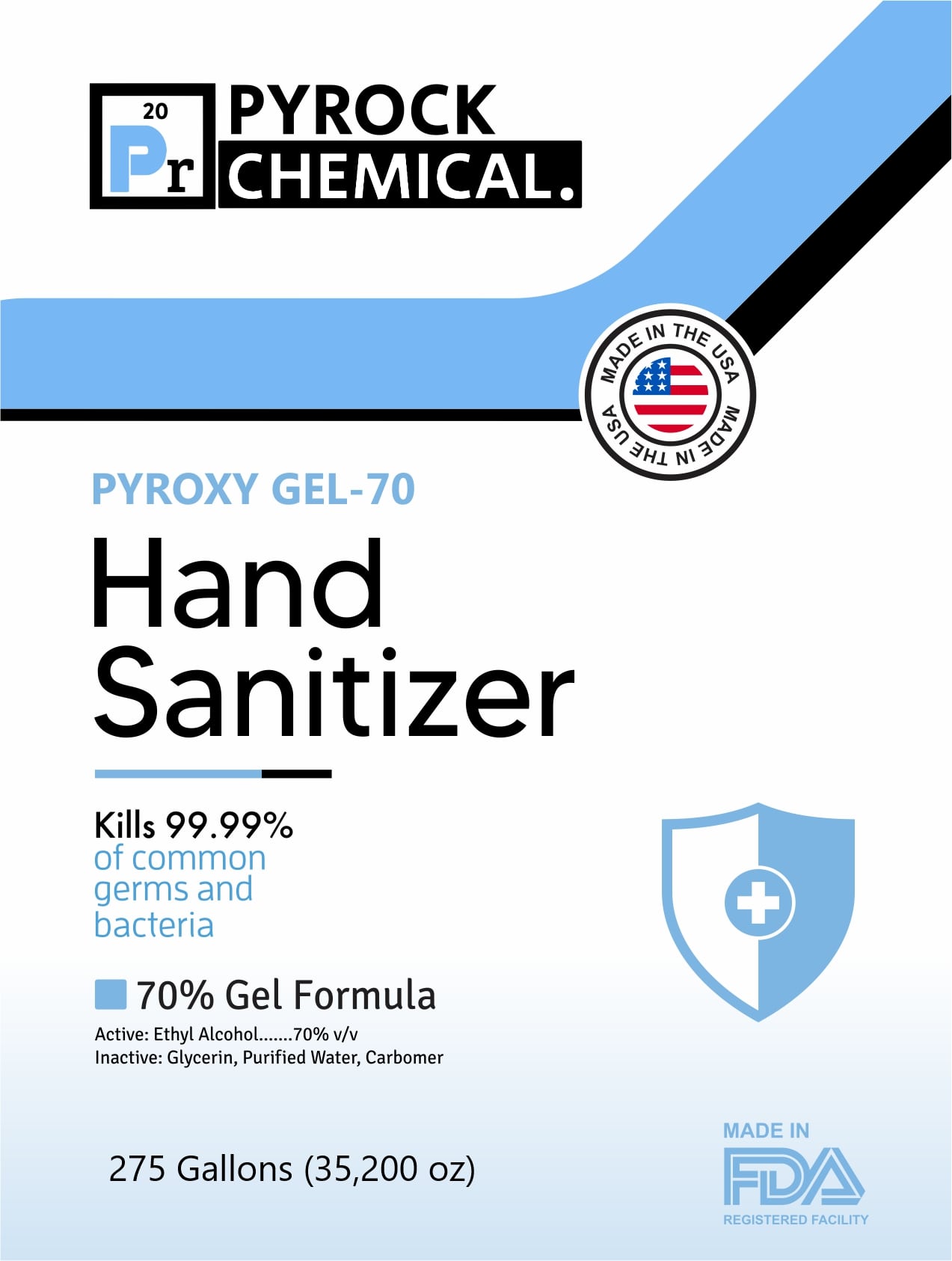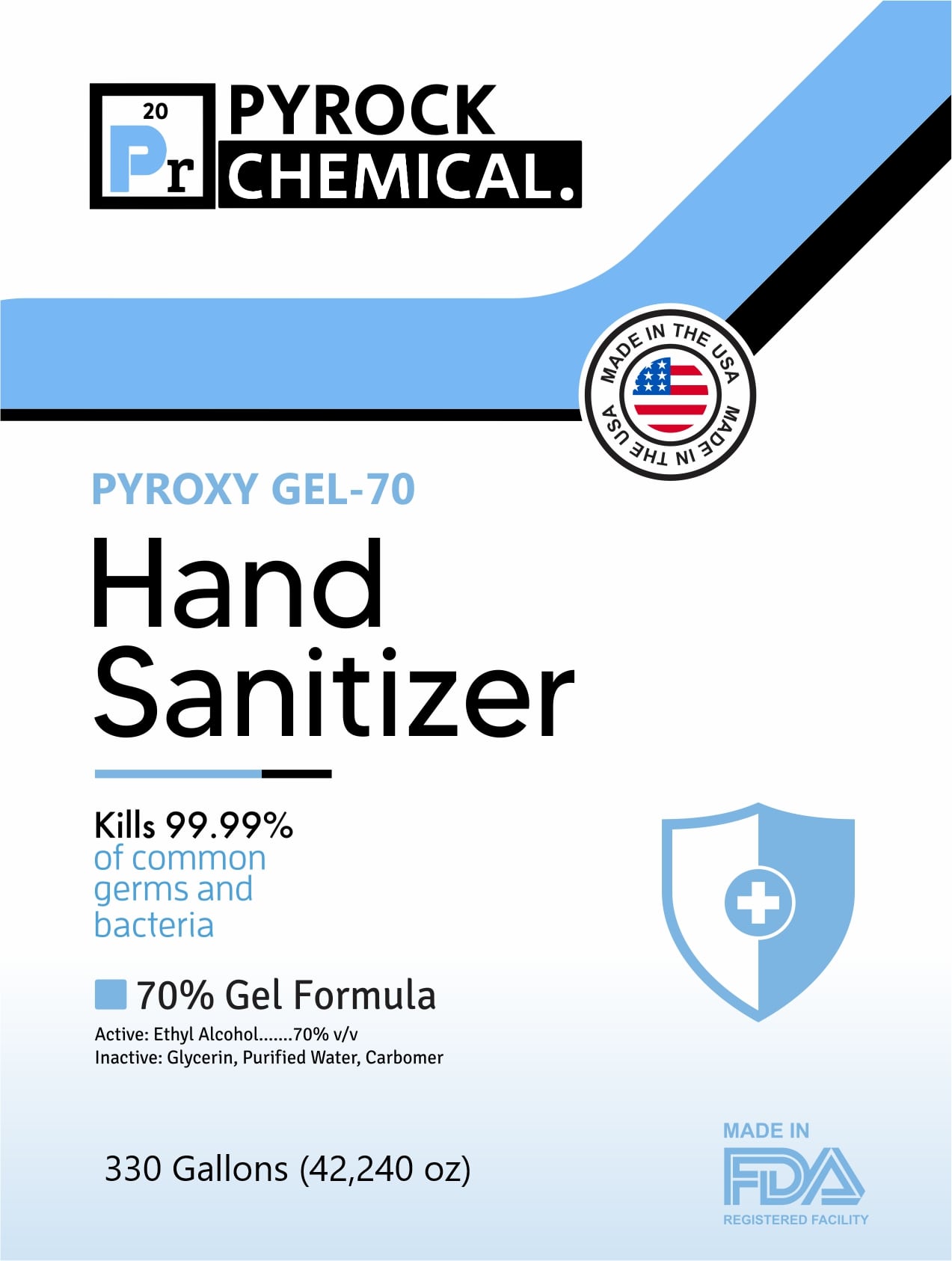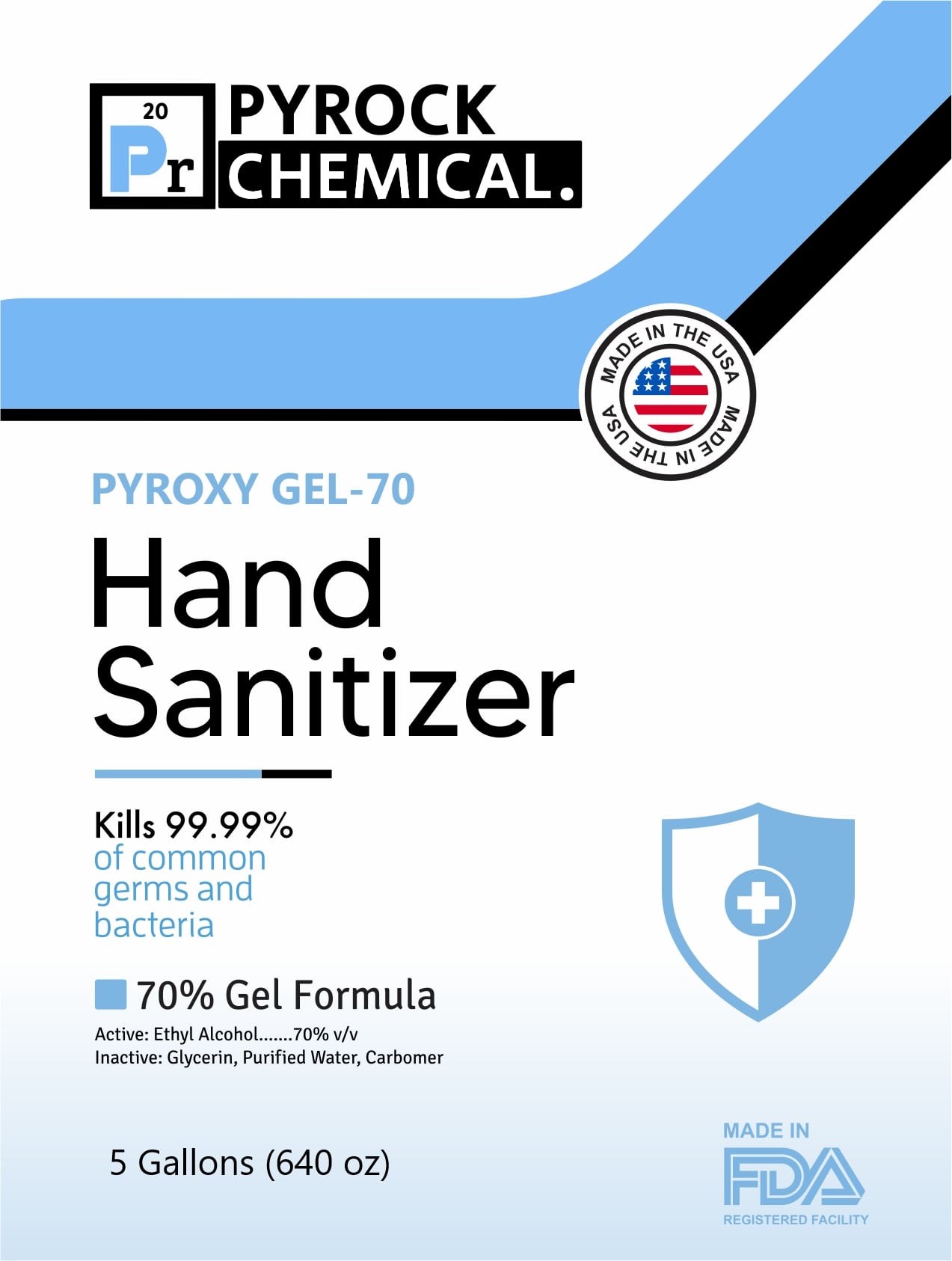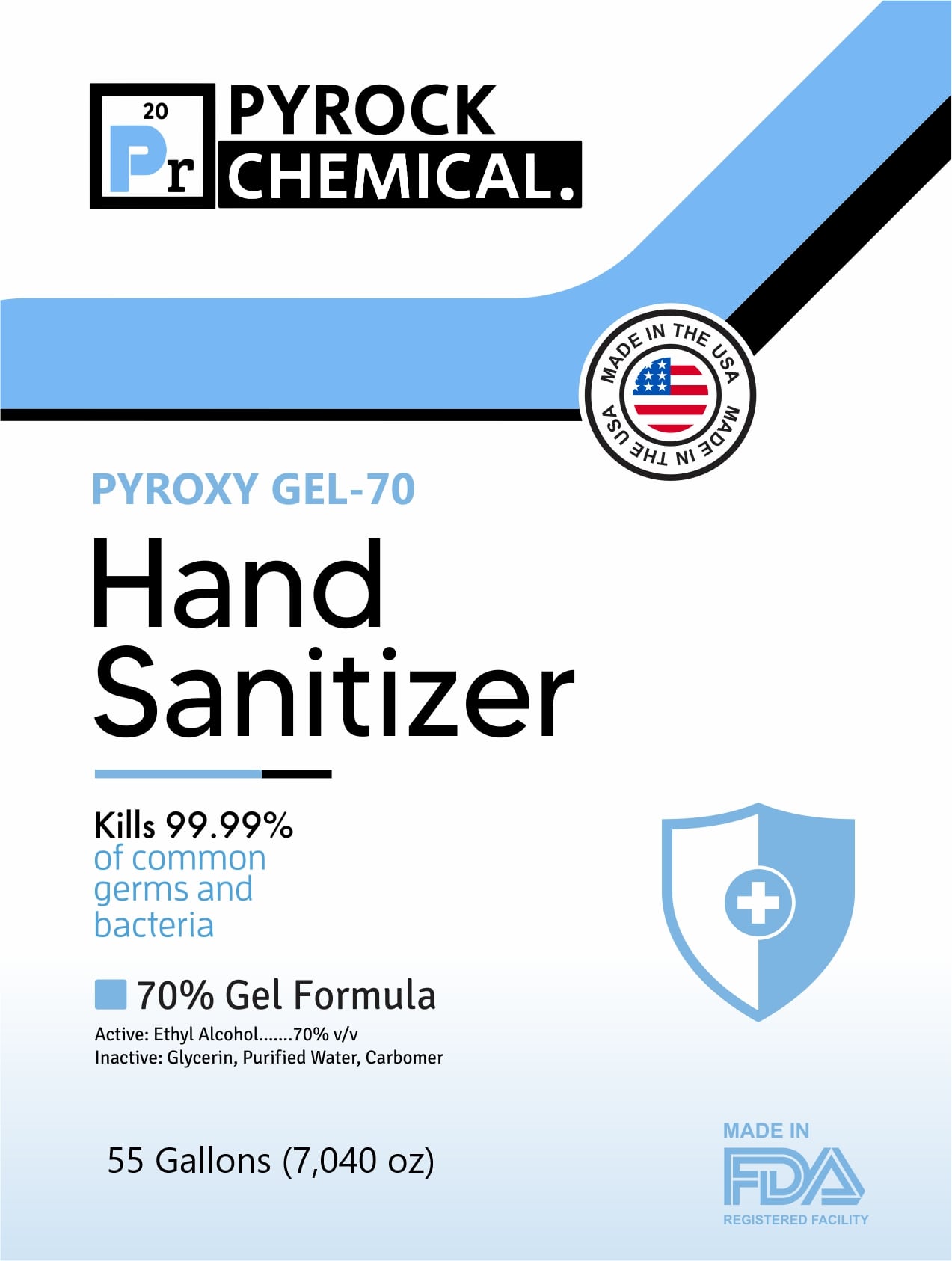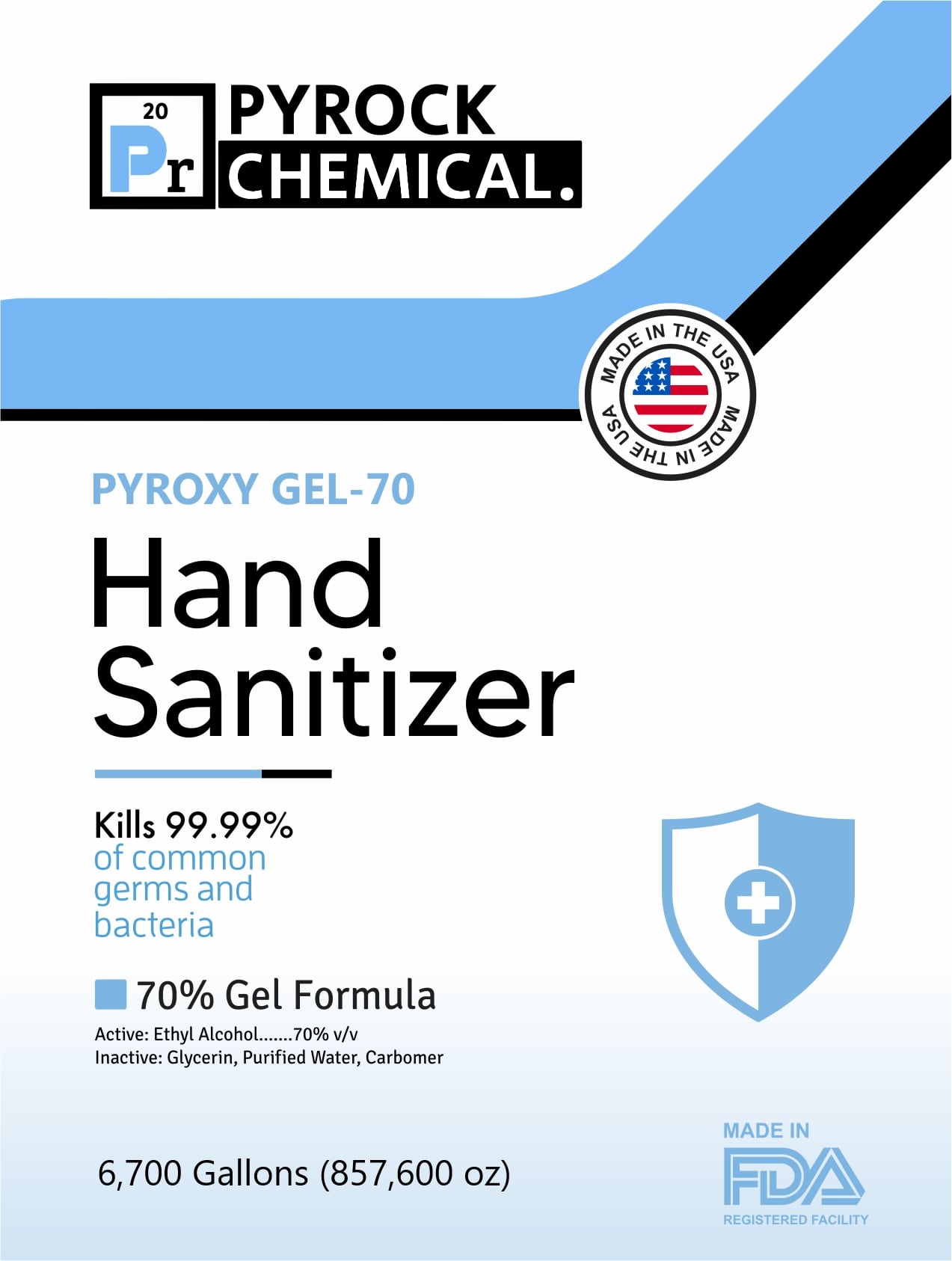 DRUG LABEL: Pyroxy Gel-70 Base
NDC: 78517-701 | Form: GEL
Manufacturer: Pyrock Chemical
Category: otc | Type: HUMAN OTC DRUG LABEL
Date: 20220130

ACTIVE INGREDIENTS: ALCOHOL 70 mL/100 mL
INACTIVE INGREDIENTS: SODIUM ACRYLOYLDIMETHYLTAURATE-ACRYLAMIDE COPOLYMER (1:1; 90000-150000 MPA.S) 1.34 mL/100 mL; GLYCERIN 2.06 mL/100 mL; WATER 26.6 mL/100 mL

Pyroxy Gel-70 Base

The hand sanitizer is manufactured in response to the COVID-19 pandemic

1. Alcohol (ethanol) (70%, volume/volume (v/v)) in an aqueous solution denatured according to Alcohol and Tobacco Tax and Trade Bureau regulations in 27 CFR part 20.
2. Glycerol (2.01% v/v).
3. Carbomber (1.33% v/v).
4. Deionized or reverse osmosis water

Active Ingredient(s)

Alcohol 70% v/v. Purpose: Antiseptic

Purpose

Antiseptic, Hand Sanitizer

Use

Hand Sanitizer to help reduce bacteria that potentially can cause disease. For use when soap and water are not available.

Warnings

For external use only. Flammable. Keep away from heat or flame

Do not use

- in children less than 2 months of age
- on open skin wounds

When using this product keep out of eyes, ears, and mouth. In case of contact with eyes, rinse eyes thoroughly with water.
Stop use and ask a doctor if irritation or rash occurs. These may be signs of a serious condition.
Keep out of reach of children. If swallowed, get medical help or contact a Poison Control Center right away.

Stop use and ask a doctor if irritation or rash occurs. These may be signs of a serious condition.

Keep out of reach of children. If swallowed, get medical help or contact a Poison Control Center right away.

Directions

- Place enough product on hands to cover all surfaces. Rub hands together until dry.
- Supervise children under 6 years of age when using this product to avoid swallowing.

Other information

- Store between 15-30C (59-86F)
- Avoid freezing and excessive heat above 40C (104F)

Inactive ingredients

glycerin, purified water, carbomer

Package Label - Principal Display Panel

18927.05 mL NDC: 78517-701-95

1249185.9 mL NDC: 78517-701-33

1040988.2 mL NDC: 78517-701-27

208197.65 mL NDC: 78517-701-55

25362259 mL NDC: 78517-701-67

3785.41 mL NDC: 78517-701-01

250 mL NDC: 78517-701-92

1000 ml NDC: 78517-701-91